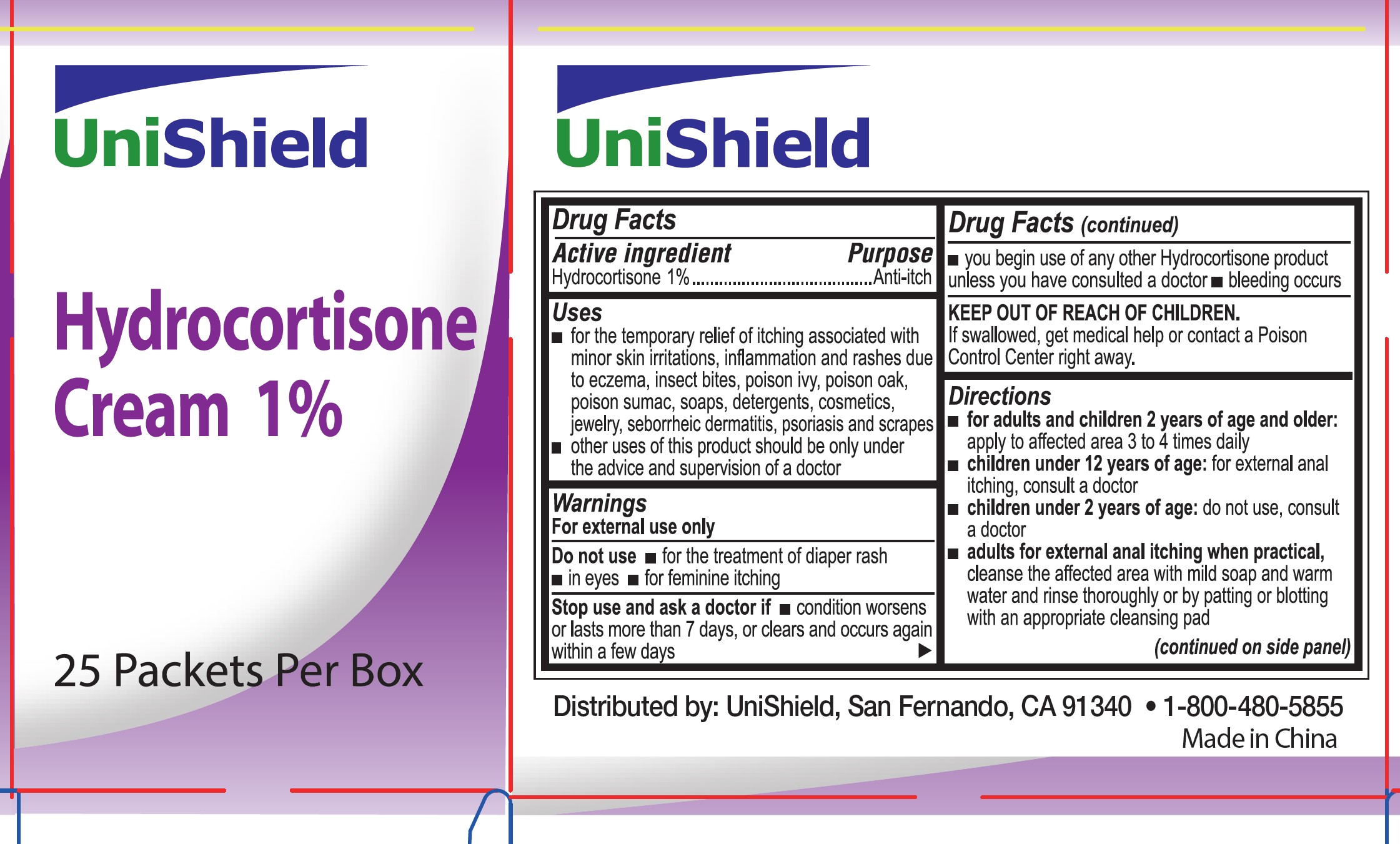 DRUG LABEL: Unishield 1%
NDC: 49314-0005 | Form: CREAM
Manufacturer: Unishield
Category: otc | Type: HUMAN OTC DRUG LABEL
Date: 20250924

ACTIVE INGREDIENTS: HYDROCORTISONE 1 g/100 g
INACTIVE INGREDIENTS: WATER; GLYCERIN; POLYOXYL 20 CETOSTEARYL ETHER; CETOSTEARYL ALCOHOL; ETHYLHEXYLGLYCERIN; MINERAL OIL; PETROLATUM; PHENOXYETHANOL

49314-0005 Unishield Hydrocortisone

Active ingredient

Hydrocortisone 1%

Purpose Anti-itch

Uses

- for temorary relief of itching associated with minor skin irritations, inflammation and rashes due to eczema, insect bites, posison ivy, poison oak, poison sumac, soaps, detergents, cosmetics, jewelry, seborrheic dermatitis, psoriasis and scrapes
- other uses of this product should be only under the advice and supervision of a doctor

Warnings

For external use only.

Do not use

- for the treatment of diaper rash
- in eyes
- for feminine itching

When using this product:

- Keep out of eyes, ears, and mouth
- In case of contact with eyes, rinse eyes throughly with water

Stop use and ask a doctor if

condition worsens or lasts more than 7 days, or clears and occurs again within a few days

you begin use of other hydrocortisone product unless you have consulted a doctor

bleeding occurs

Keep out of reach of children. If swallowed, get medical help or contact a Poison Control Center right away.

Directions

- For adults and children 2 years of age and older: apply to affected area 3 to 4 times daily
- children under 12 years of age: for external anal itching, consult a doctor
- children under 2 years of age: do not use, consult a doctor
- adults for external anal itching when practical, cleanse the affected area with mild soap and warm water and rinse thoroughly or by patting or blotting with an appropriate cleansing pad
- gently dry by patting or blotting with toilet tissue or a soft cloth before application of this product

Other information

- Store at room temperature (do not freeze)
- Tamper evident, do not use any opened or torn packets

Inactive ingredients

cetearyl alcohol, ceteareth-20, ethylhexylglycerin, glycerin, glycerol fatty acid ester, mineral oil, petrolactum, phenoxyethanol, water